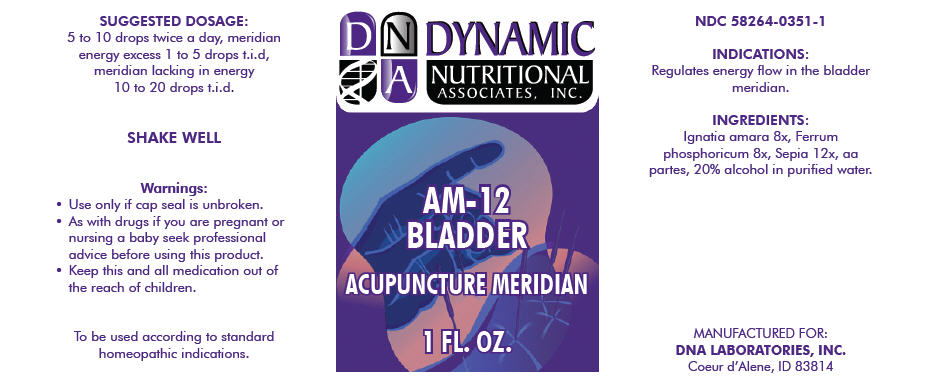 DRUG LABEL: AM-12
NDC: 58264-0351 | Form: SOLUTION
Manufacturer: DNA Labs, Inc.
Category: homeopathic | Type: HUMAN OTC DRUG LABEL
Date: 20250109

ACTIVE INGREDIENTS: STRYCHNOS IGNATII WHOLE 8 [hp_X]/1 mL; FERROSOFERRIC PHOSPHATE 8 [hp_X]/1 mL; SEPIA OFFICINALIS JUICE 12 [hp_X]/1 mL
INACTIVE INGREDIENTS: ALCOHOL; WATER

AM-12

NDC 58264-0351-1

INDICATIONS

PURPOSE

Regulates energy flow in the bladder meridian.

INGREDIENTS

INACTIVE INGREDIENT

Ignatia amara 8x, Ferrum phosphoricum 8x, Sepia 12x, aa partes, 20% alcohol in purified water.

SUGGESTED DOSAGE

5 to 10 drops twice a day, meridian energy excess 1 to 5 drops t.i.d, meridian lacking in energy 10 to 20 drops t.i.d.

STORAGE AND HANDLING

SHAKE WELL

Warnings

- Use only if cap seal is unbroken.

PREGNANCY OR BREAST FEEDING

- As with drugs if you are pregnant or nursing a baby seek professional advice before using this product.

KEEP OUT OF REACH OF CHILDREN

- Keep this and all medication out of the reach of children.

To be used according to standard homeopathic indications.

PRINCIPAL DISPLAY PANEL - 1 FL. OZ. Bottle Label

DYNAMIC
NUTRITIONAL
ASSOCIATES, INC.

AM-12
BLADDER

ACUPUNCTURE MERIDIAN

1 FL. OZ.